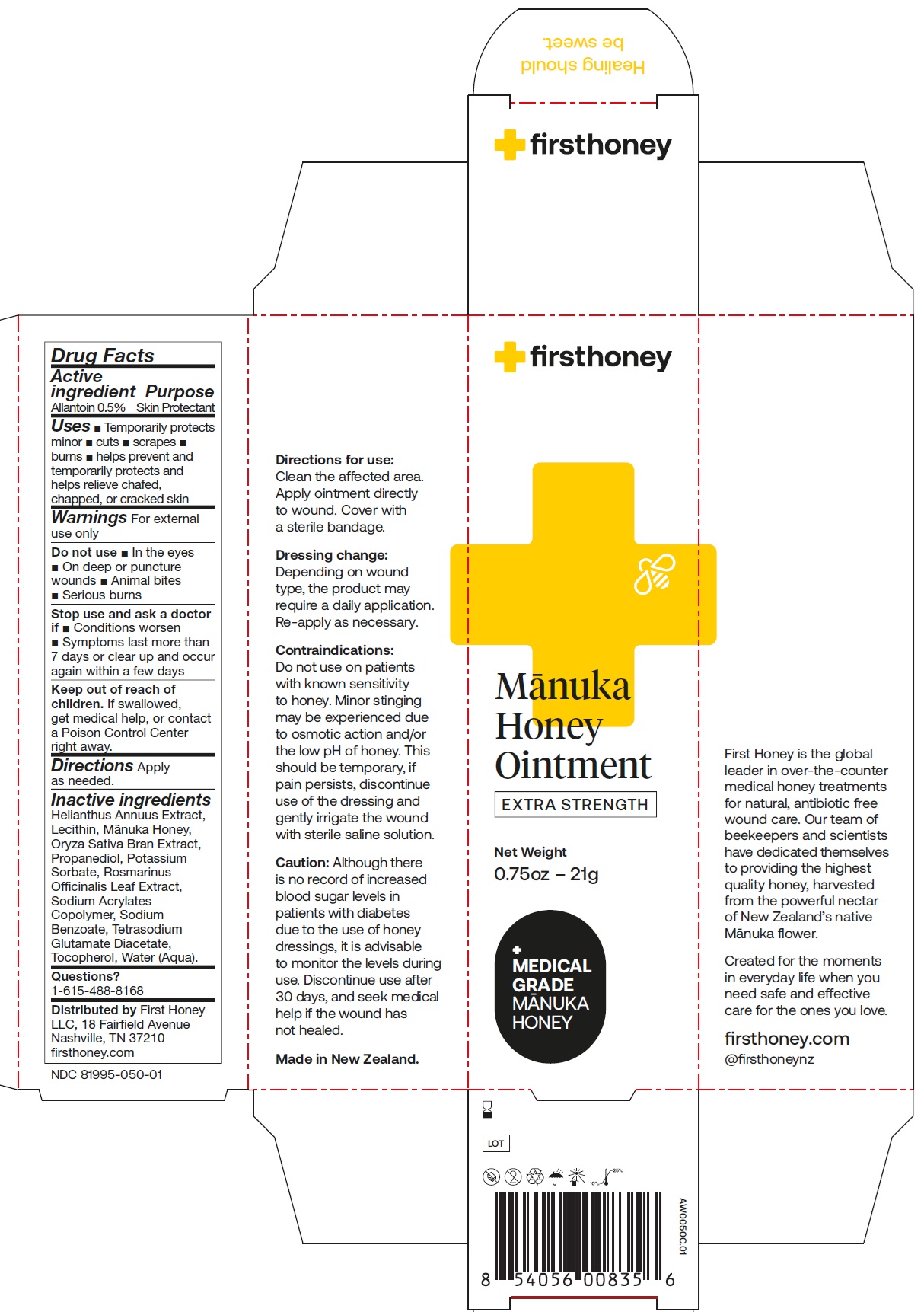 DRUG LABEL: Manuka Honey Extra Strength
NDC: 81995-050 | Form: GEL
Manufacturer: First Honey LLC
Category: otc | Type: HUMAN OTC DRUG LABEL
Date: 20250204

ACTIVE INGREDIENTS: ALLANTOIN 5 mg/1 g
INACTIVE INGREDIENTS: PROPANEDIOL; POTASSIUM SORBATE; ROSEMARY; SODIUM BENZOATE; TETRASODIUM GLUTAMATE DIACETATE; TOCOPHEROL; WATER

Manuka Honey Ointment Extra Strength

Active ingredient

Allantoin 0.5%

Purpose

Skin Protectant

Uses

- Temporarily protects minor
- cuts
- scrapes
- burns
- helps prevent and temporarily protects and helps relieve chafed, chapped, or cracked skin

Warnings

For external use only

Do not use

- In the eyes
- On deep or puncture wounds
- Animal bites
- Serious burns

Stop use and ask a doctor if

- Conditions worsen
- Symptoms last more than 7 days or clear up and occur again within a few days

Keep out of reach of children.

If swallowed, get medical help, or contact a Poison Control Center right away.

Directions

Apply as needed.

Inactive ingredients

Helianthus Annuus Extract, Lecithin, Mãnuka Honey, Oryza Sativa Bran Extract, Propanediol, Potassium Sorbate, Rosmarinus Officinalis Leaf Extract, Sodium Acrylates Copolymer, Sodium Benzoate, Tetrasodium Glutamate Diacetate, Tocopherol, Water (Aqua).

Questions?

1-615-488-8168